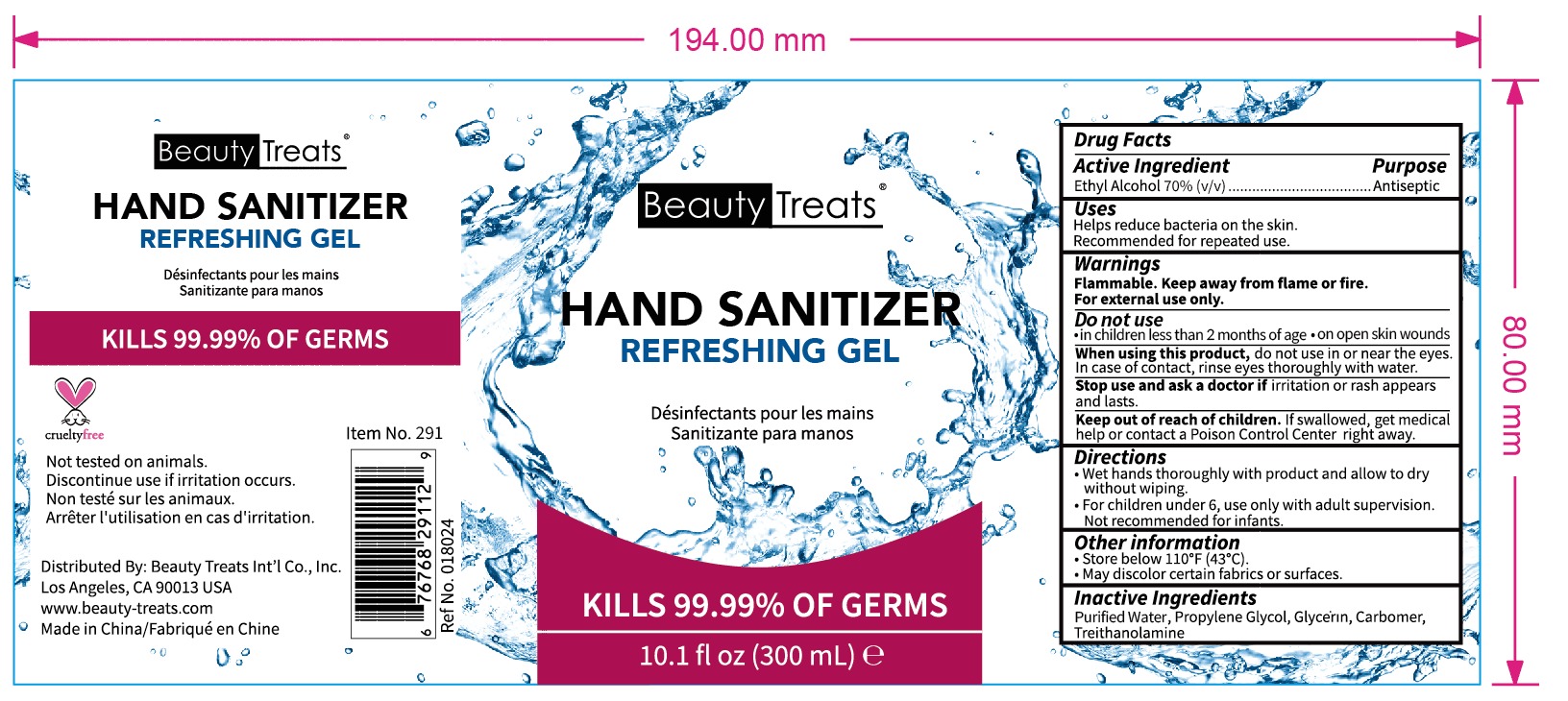 DRUG LABEL: BeautyTreats HAND SANITIZER
NDC: 74765-014 | Form: GEL
Manufacturer: Zhejiang Yiwu Limei Cosmetics Co., Ltd
Category: otc | Type: HUMAN OTC DRUG LABEL
Date: 20200510

ACTIVE INGREDIENTS: ALCOHOL 70 mL/100 mL
INACTIVE INGREDIENTS: GLYCERIN; TROLAMINE; WATER; PROPYLENE GLYCOL; CARBOMER 980

NA

Active Ingredient(s)

Ethyl Alcohol 70% v/v. Purpose: Antiseptic

Purpose

Antiseptic, Hand Sanitizer

Use

Helps reduce bacteria on the skin. Recommended for repeated use.

Warnings

Flammable. Keep away from heat or flame, For external use only.

Do not use

- in children less than 2 months of age
- on open skin wounds

When using this product do not use in or near the eyes. In case of contact,, rinse eyes thoroughly with water.
Stop use and ask a doctor if irritation or rash appears and lasts.
Keep out of reach of children. If swallowed, get medical help or contact a Poison Control Center right away.

Stop use and ask a doctor if irritation or rash occurs. These may be signs of a serious condition.

Keep out of reach of children. If swallowed, get medical help or contact a Poison Control Center right away.

Directions

- Wet hands thoroughly with product and allow to dry without wiping.
- for children under 6, use only with adult supervision. not recommended for infants.

Other information

- Store between 110F(43C)
- May discolor certain fabrics of surfaces.

Inactive ingredients

purified water,glycerin,propylene glycol, carbomer,triethanolamine

Package Label - Principal Display Panel

60 mL NDC: 074765-014-01

300 mL NDC: 074765-014-02